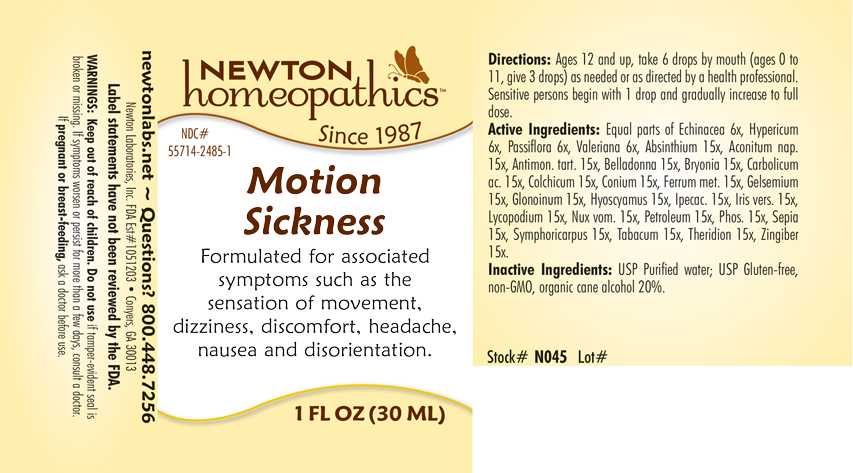 DRUG LABEL: Motion Sickness
NDC: 55714-2485 | Form: LIQUID
Manufacturer: Newton Laboratories, Inc.
Category: homeopathic | Type: HUMAN OTC DRUG LABEL
Date: 20250207

ACTIVE INGREDIENTS: ACONITUM NAPELLUS 15 [hp_X]/1 mL; ANTIMONY POTASSIUM TARTRATE 15 [hp_X]/1 mL; ATROPA BELLADONNA 15 [hp_X]/1 mL; BRYONIA ALBA ROOT 15 [hp_X]/1 mL; PHENOL 15 [hp_X]/1 mL; COLCHICUM AUTUMNALE BULB 15 [hp_X]/1 mL; CONIUM MACULATUM FLOWERING TOP 15 [hp_X]/1 mL; IRON 15 [hp_X]/1 mL; GELSEMIUM SEMPERVIRENS ROOT 15 [hp_X]/1 mL; NITROGLYCERIN 15 [hp_X]/1 mL; HYOSCYAMUS NIGER 15 [hp_X]/1 mL; IPECAC 15 [hp_X]/1 mL; IRIS VERSICOLOR ROOT 15 [hp_X]/1 mL; LYCOPODIUM CLAVATUM SPORE 15 [hp_X]/1 mL; STRYCHNOS NUX-VOMICA SEED 15 [hp_X]/1 mL; KEROSENE 15 [hp_X]/1 mL; PHOSPHORUS 15 [hp_X]/1 mL; SEPIA OFFICINALIS JUICE 15 [hp_X]/1 mL; SYMPHORICARPOS ALBUS FRUIT 15 [hp_X]/1 mL; TOBACCO LEAF 15 [hp_X]/1 mL; HYPERICUM PERFORATUM 6 [hp_X]/1 mL; GINGER 15 [hp_X]/1 mL; VALERIAN 6 [hp_X]/1 mL; ECHINACEA, UNSPECIFIED 6 [hp_X]/1 mL; PASSIFLORA INCARNATA FLOWERING TOP 6 [hp_X]/1 mL; WORMWOOD 15 [hp_X]/1 mL; THERIDION CURASSAVICUM 15 [hp_X]/1 mL
INACTIVE INGREDIENTS: WATER; ALCOHOL

Motion 2485L

INDICATIONS & USAGE SECTION

Formulated for associated symptoms such as the sensation of movement, dizziness, discomfort, headache, nausea and disorientation.

DOSAGE & ADMINISTRATION SECTION

Directions: Ages 12 and up, take 6 drops by mouth (ages 0 to 11, give 3 drops) as needed or as directed bh a health professional. Sensitive persons begin with 1 drop and gradually increase to full dose.

OTC - ACTIVE INGREDIENT SECTION

Equal parts of Echinacea 6x, Hypericum perforatum 6x, Passiflora incarnata 6x, Valeriana officinalis 6x, Absinthium 15x, Aconitum napellus 15x, Antimonium tartaricum 15x, Belladonna 15x, Bryonia 15x, Carbolicum acidum 15x, Colchicum autumnale 15x, Conium maculatum 15x, Ferrum metallicum 15x, Gelsemium sempervirens 15x, Glonoinum 15x, Hyoscyamus niger 15x, Ipecacuanha 15x, Iris versicolor 15x, Lycopodium clavatum 15x, Nux vomica 15x, Petroleum 15x, Phosphorus 15x, Sepia 15x, Symphoricarpus racemosus 15x, Tabacum 15x, Theridion 15x, Zingiber officinale 15x.

OTC - PURPOSE SECTION

Formulated for associated symptoms such as the sensation of movement, dizziness, discomfort, headache, nausea and disorientation.

INACTIVE INGREDIENT SECTION

Inactive Ingredients: USP Purified Water; USP Gluten-free, non-GMO, organic cane alcohol 20%.

QUESTIONS SECTION

newtonlabs.net – Questions? 800.448.7256

Newton Laboratories, Inc. FDA Est # 1051203 - Conyers, GA 30013

WARNINGS SECTION

WARNINGS: Keep out of reach of children. Do not use if tamper-evident seal is broken or missing. If symptoms worsen or persist for more than a few days, consult a doctor. If pregnant or breast-feeding, ask a doctor before use.

OTC - PREGNANCY OR BREAST FEEDING SECTION

If pregnant or breast-feeding, ask a doctor before use.

OTC - KEEP OUT OF REACH OF CHILDREN SECTION

Keep out of reach of children.